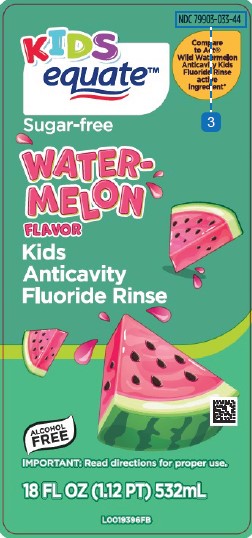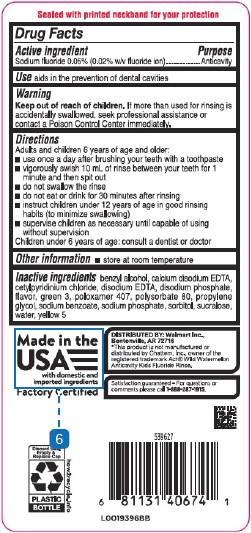 DRUG LABEL: Anticavity
NDC: 79903-033 | Form: RINSE
Manufacturer: Walmart Inc.
Category: otc | Type: HUMAN OTC DRUG LABEL
Date: 20260227

ACTIVE INGREDIENTS: SODIUM FLUORIDE 0.2 mg/1 mL
INACTIVE INGREDIENTS: CETYLPYRIDINIUM CHLORIDE; BENZYL ALCOHOL; EDETATE CALCIUM DISODIUM ANHYDROUS; EDETATE DISODIUM ANHYDROUS; SODIUM PHOSPHATE, DIBASIC, ANHYDROUS; FD&C GREEN NO. 3; POLOXAMER 407; POLYSORBATE 80; PROPYLENE GLYCOL; SODIUM BENZOATE; SODIUM PHOSPHATE; SORBITOL; SUCRALOSE; WATER; FD&C YELLOW NO. 5

Equate 201.000/201AA
Anticavity rinse watermelon

TAMPER EVIDENT STATEMENT

Sealed with printed neckband for your protection

Active ingredient

Sodium fluoride 0.05% (0.02% w/v fluoride ion)

Purpose

Anticavity

Use

aids in the prevention of dental cavities

Warnings

for this product

Keep out of reach of children.

If more than used for rinsing is accidentally swallowed, seek professional assistance or contact a Poison Control Center immediately.

Directions

Adults and children 6 years and older:

- use once a day after brushing your teeth with toothpaste
- vigorously swish 10 milliliters of rinse between your teeth for 1 minute and then spit out
- do not swallow the rinse
- do not eat or drink for 30 minutes after rinsing
- instruct children under 12 years of age in good rinsing habits (to minimize swallowing)
- supervise children as necessary unitl capable of using without supervision

Children under 6 years of age: consult a dentist or doctor

Other information

- store at room temperature

Inactive ingredients

benzyl alcohol, calcium disodium EDTA, cetylpyridinium chloride, disodium EDTA, disodium phosphate, flavor, green 3, poloxamer 407, polysorbate 80, propylene glycol, sodium benzoate, sodium phosphate, sorbitol, sucralose, water, yellow 5

Disclaimer

*This product is not manufactured or distributed by Chattem, Inc., owner of the registered trademark Act® Wild Watermelon Anticavity Kids Fluoride Rinse.

Adverse reaction

Distributed by: Walmart Inc.,

Bentonville, AR 72716

Made in the USA with domestic and imported ingredients

Factory Certified

Satisfaction guaranteed - For questions or comments please call 1-888-287-1915.

Discard Seal, Empty & Replace Cap

PLASTIC BOTTLE

how2recycle.info

principal display panel

NDC 79903-033-44

KIDS equate™

Compare to Act® Wild Watermelon Anticavity Kids Fluoride Rinse active ingredient*

Sugar-free

WATERMELON FLAVOR

Kids Anticavity Fluoride Rinse

Alcohol FREE

IMPORTANT: Read directions for proper use

18 FL OZ (1.12 PT) 532 mL